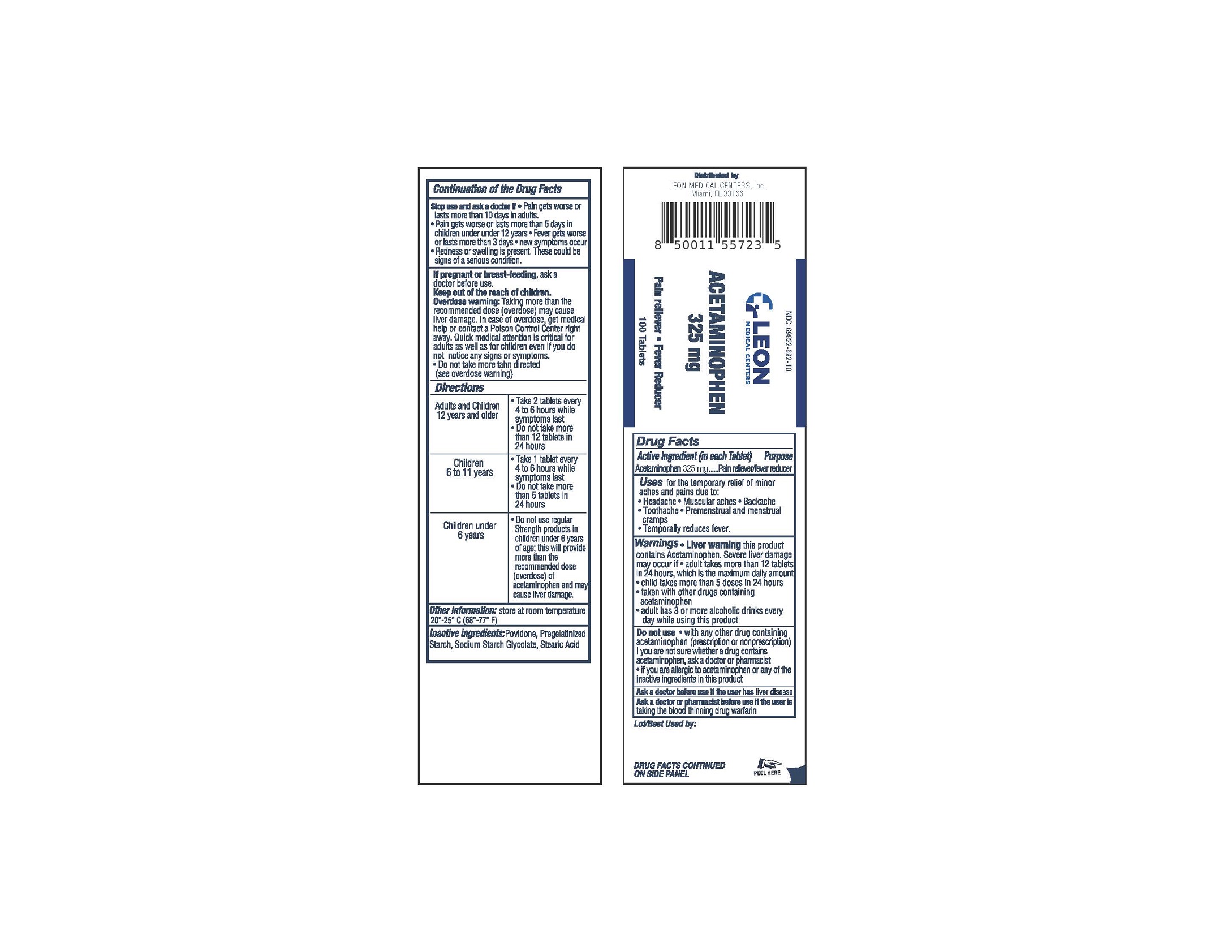 DRUG LABEL: Acetaminophen
NDC: 69822-692 | Form: TABLET
Manufacturer: Southern Sales & Service, Inc.
Category: otc | Type: HUMAN OTC DRUG LABEL
Date: 20231129

ACTIVE INGREDIENTS: ACETAMINOPHEN 325 mg/1 1
INACTIVE INGREDIENTS: POVIDONE; STARCH, CORN; SODIUM STARCH GLYCOLATE TYPE A CORN; STEARIC ACID

Acetaminophen

Active Ingredient (in each Tablet)

Acetaminophen 325 mg

Purpose

Pain reliever/fever reducer

Uses

for the temporary relief of minor aches and pains due to:

Headache

Muscular aches

Backache

Toothache

Premenstrual and menstrual cramps

Temporally reduces fever.

• Liver warning Warnings

this product contains Acetaminophen. Severe liver damage may occur if

- adult takes more than 12 tablets in 24 hours, which is the maximum daily amount
- child takes more than 5 doses in 24 hours
- taken with other drugs containing acetaminophen
- adult has 3 or more alcoholic drinks every day while using this product

Do not use

- with any other drug containing acetaminophen (prescription or nonprescription)
- you are not sure whether a drug contains acetaminophen, ask a doctor or pharmacist
- if you are allergic to acetaminophen or any of the inactive ingredients in this product

Ask a doctor before use if the user has

liver disease

Ask a doctor or pharmacist before use if the user is

taking the blood thinning drug warfarin

Stop use and ask a doctor if

Pain gets worse or lasts more than 10 days in adults.

Pain gets worse or lasts more than 5 days in children under under 12 years

Fever gets worse or last more than 3 days

new symptoms occur

Redness or swelling is present. These could be signs of a serious condition.

If pregnant or breast-feeding,

ask a doctor before use.

Keep out of the reach of children.

Overdose warning:

Taking more than the recommended dose (overdose) may cause liver damage. In case of overdose, get medical help or contact a Poison Control Center right away. Quick medical attention is critical for adults as well as for children even if you do not notice any signs or syptoms.

- Do not take more tahn directed (see overdose warning)

Directions

Adults and Children; 12 years and older | Take 2 tablets every 4 to 6 hours while symptoms last; Do not take more than 12 tablets in 24 hours
Children; 6 to 11 years | Take 1 tablet every 4 to 6 hours while symptoms last; Do not take more than 5 tablets in 24 hours
Children under; 6 years | Do not use regular Strength products in children uder 6 years of age; this will provide more than the recommended dose (overdose) of acetaminophen and may cause liver damage.

Other information

store at room temperature 20°-25°C (68-77°F)

Inactive Ingredients

Povidone, Pregelatinized Starch, Sodium Starch Glycolate, Stearic Acid